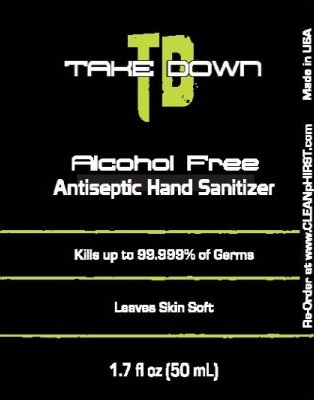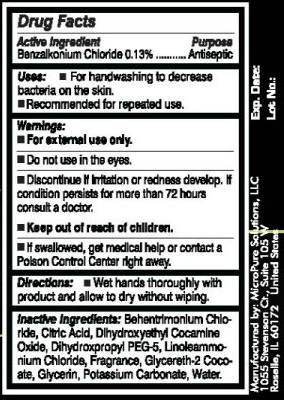 DRUG LABEL: TD Take Down Alcohol Free Antiseptic Hand Sanitizer
NDC: 52138-200 | Form: GEL
Manufacturer: Cleanphirst, LLC
Category: otc | Type: HUMAN OTC DRUG LABEL
Date: 20100603

ACTIVE INGREDIENTS: BENZALKONIUM CHLORIDE 0.13 mL/100 mL
INACTIVE INGREDIENTS: BEHENTRIMONIUM CHLORIDE; CITRIC ACID MONOHYDRATE; DIHYDROXYETHYL COCAMINE OXIDE; GLYCERETH-2 COCOATE; GLYCERIN; POTASSIUM CARBONATE; WATER

Take Down TD Alcohol Free Antiseptic Hand Sanitizer

Active Ingredient Purpose

Benzalkonium Chloride 0.13 percent.............................Antiseptic

Uses

For hand washing to decrease bacteria on the skin.

Recommended for repeated use.

WARNINGS

Warnings: For external use only. Do not use in the eyes. Discontinue if irritation or redness develop. If condition persists for more than 72 hours consult a doctor. Keep out of reach of children. If swallowed, get medical help or contact a Poison Control Center right away.

DOSAGE AND ADMINISTRATION

Directions: Wet hands thoroughly with product and allow to dry without wiping.

INACTIVE INGREDIENT

Inactive Ingredients: Behentrimonium Chloride, Citric Acid, Dihydroxyethyl Cocamine Oxide, Dihydroxpropyl PEG-5, Linoleammonium Chloride, Fragrance, Glycereth-2 Cocoate, Glycerin, Potassium Carbonate, Water.

PACKAGE LABEL

TD Take down Alcohol Free Antiseptic Hand Sanitizer Kills up to 99.999 percent of germs leaves skin soft 1.7fl oz (50mL) Re-Order at www.CLEANpHIRST.com Made in USA Manufactured by: MicroPure Solutions, LLC 1055 Stevenson Ct., Suite 15 W Roselle, IL 60172 United States Exp. Date: Lot No.: